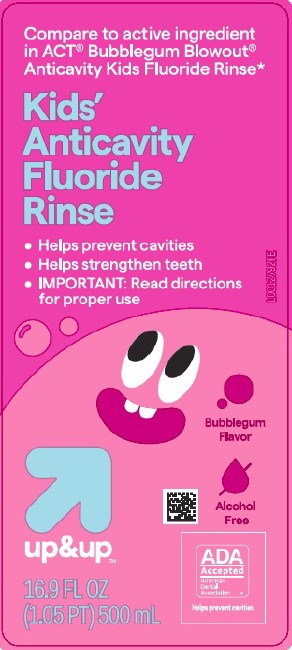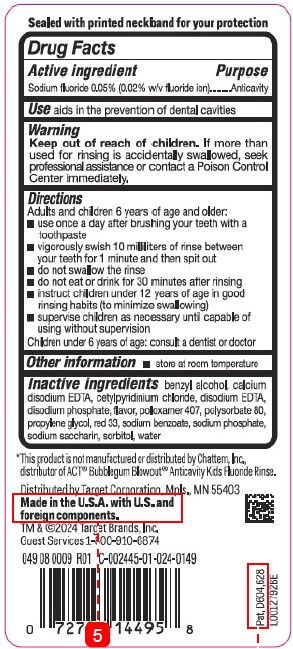 DRUG LABEL: Anticavity
NDC: 11673-004 | Form: RINSE
Manufacturer: Target Corporation
Category: otc | Type: HUMAN OTC DRUG LABEL
Date: 20260218

ACTIVE INGREDIENTS: SODIUM FLUORIDE 0.2 mg/1 mL
INACTIVE INGREDIENTS: BENZYL ALCOHOL; EDETATE CALCIUM DISODIUM ANHYDROUS; CETYLPYRIDINIUM CHLORIDE; EDETATE DISODIUM; SODIUM PHOSPHATE, DIBASIC, ANHYDROUS; POLOXAMER 407; POLYSORBATE 80; PROPYLENE GLYCOL; D&C RED NO. 33; SODIUM BENZOATE; SODIUM PHOSPHATE; SACCHARIN SODIUM; SORBITOL; WATER

Up & Up 004.002/004AE
Anticavity Fluoride Rinse, Bubble Gum

Tamper Evident Statement

Saftey sealed with printed neckband for your protection

Active ingredient

Sodium fluoride 0.05% (0.02% w/v fluoride ion)

Purpose

Anticavity

Use

aids in the prevention of dental cavities

Warnings

for this product

Keep out of reach of children.

If more than used for rinsing is accidentally swallowed, seek professional assistance or contact a Poison Control Center immediately.

Directions

Adults and children 6 years of age and older:

- use once a day after brushing your teeth with toothpaste
- vigorously swish 10 mililiters of rinse between your teeth for 1 minute and then spit out
- do not swallow the rinse
- do not eat or drink for 30 minutes after rinsing
- instruct children under 12 years of age in good rinsing habits (to minimize swallowing)
- supervise children as necessary until capable of using without supervision

Children under 6 years of age: consult a dentist or doctor

Other information

- store at room temperature

Inactive ingredients

benzyl alcohol, calcium disodium EDTA, cetylpyridinium chloride, disodium EDTA, disodium phosphate, flavor, poloxamer 407, polysorbate 80, propylene glycol, red 33, sodium benzoate, sodium phosphate, sodium saccharin, sorbitol, water

Disclaimer

*This product is not manufactured or distributed by Chattem, Inc., distributor of ACT®Bubblegum Blowout® Anticavity Kids Fluoride Rinse.

Adverse reaction

Distributed by Target Corporation Mpls., MN 55403

Made in the U.S.A. with U.S. and foreign components.

TM & ©2024 Target Brands, Inc.

Guest Services 1-800-910-6874

049 08 0009 R01 C-002445-01-024-0149

Pat. D604,628

Principal display panel

Compare to active ingredient in ACT®Bubblegum Blowout®Anticavity Kids Fluoride Rinse*

Kids' Anticavity Fluoride Rinse

- Helps prevent cavities
- Helps strengthen teeth
- IMPORTANT: read directions for proper use

Bubblegum Flavor

Alcohol free

up & up ™

ADA Accepted

American Dental Association

Helps prevent cavities

16.9 FL OZ (1.05 PT) 500 mL